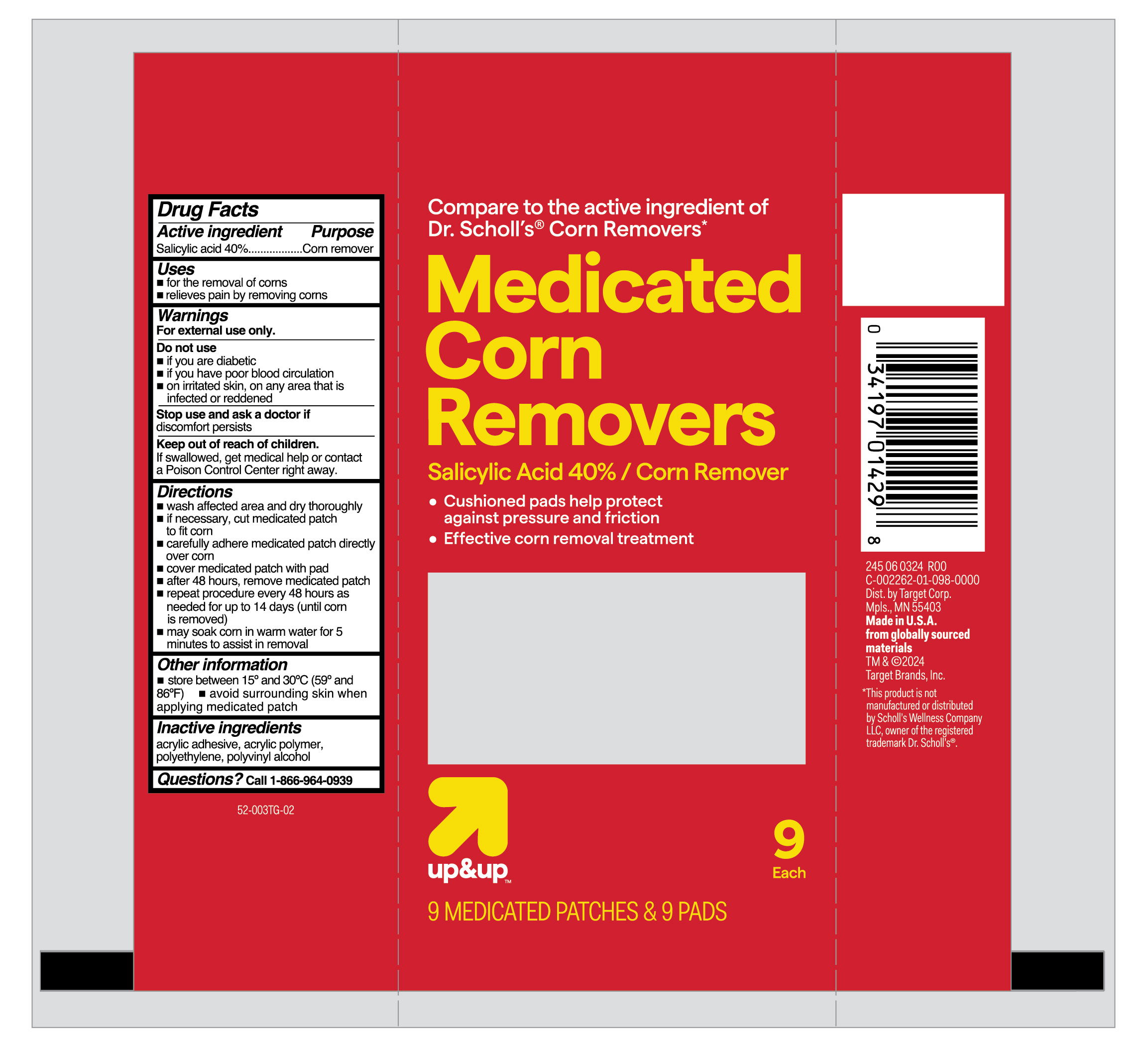 DRUG LABEL: Salicylic Acid
NDC: 82442-400 | Form: PATCH
Manufacturer: Target Corporation
Category: otc | Type: HUMAN OTC DRUG LABEL
Date: 20251231

ACTIVE INGREDIENTS: SALICYLIC ACID 400 mg/1 g
INACTIVE INGREDIENTS: POLYVINYL ALCOHOL; HIGH DENSITY POLYETHYLENE

Target Medicated Corn Removers

Active ingredient

Salicylic acid 40%

Purpose

Corn remover

Uses

- for the removal of corns
- relieves pain by removing corns

Warnings

For external use only.

Do not use

- if you are diabetic
- if you have poor blood circulation
- on irritated skin, or any area that is infected or reddened

Stop use and ask a doctor if

discomfort persists

Keep out of reach of children.

If swallowed, get medical help or contact a Poison Control Center right away.

Directions

- wash affected area and dry thoroughly
- if necessary, cut medicated patch to fit corn
- carefully adhere medicated patch directly over corn
- cover medicated patch with pad
- after 48 hours, remove medicated patch
- repeat procedure every 48 hours as needed for up to 14 days (until corn is removed)
- may soak corn in warm water for 5 minutes to assist in removal

Other information

- store between 15°C to 30°C (59°F to 86°F)
- avoid surrounding skin when applying medicated patch

Inactive ingredients

acrylic adhesive, acrylic polymer, polyethylene, polyvinyl alcohol

Questions?

call 1-866-964-0939

RECENT MAJOR CHANGES

.

Principal Display Panel

Compare to the active ingredient of

Dr. Scholl's Corn Removers

Medicated

Corn

Removers

Salicylic acid 40% / Corn Remover

- Cushioned pads help protect

against pressure and friction

- Effective corn removal treatment

up&up 9 each

9 MEDICATED PATCHES & 9 PADS